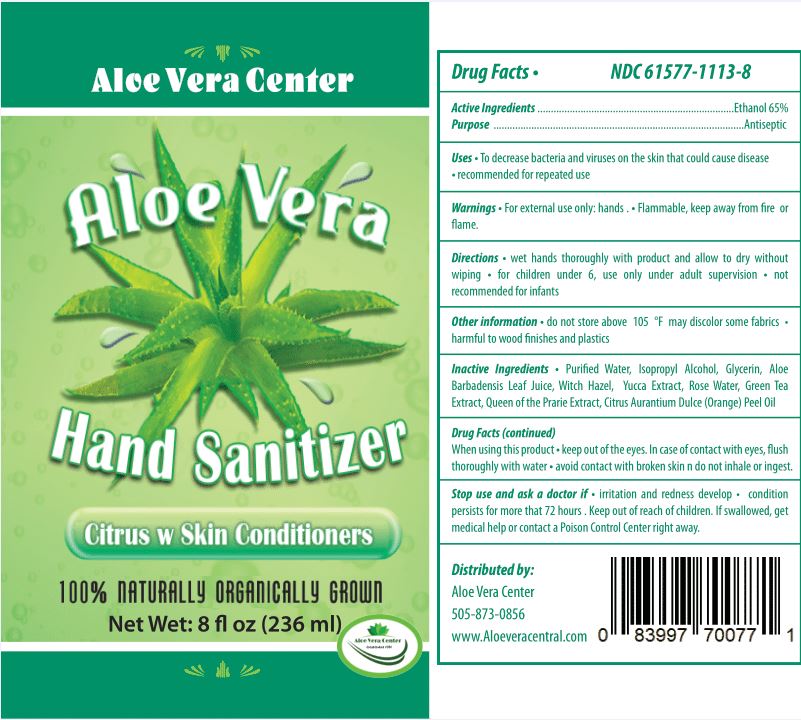 DRUG LABEL: ALOE VERA CENTER HAND SANITIZER
NDC: 61577-1113 | Form: GEL
Manufacturer: SOMBRA COSMETICS
Category: otc | Type: HUMAN OTC DRUG LABEL
Date: 20200723

ACTIVE INGREDIENTS: ALCOHOL 65 mL/100 mL
INACTIVE INGREDIENTS: WATER; GLYCERIN; ISOPROPYL ALCOHOL; ROSA DAMASCENA FLOWER; WITCH HAZEL; ORANGE OIL; CAMELLIA SINENSIS FLOWER; FILIPENDULA ULMARIA WHOLE; AMMONIUM ACRYLOYLDIMETHYLTAURATE, DIMETHYLACRYLAMIDE, LAURYL METHACRYLATE AND LAURETH-4 METHACRYLATE COPOLYMER, TRIMETHYLOLPROPANE TRIACRYLATE CROSSLINKED (45000 MPA.S); YUCCA SCHIDIGERA STEM

Aloe Vera Center Hand Sanitizer

Active Ingredients

Ethyl Alcohol 65%

Uses

Helps reduce bacteria on the skin that could cause diseases.

Warnings

Flammable. Keep away from fire or flame. For external use only.

Do not use

When using this product, do not use in or near the eyes. In case of contact, rinse eyes thoroughly with water.

When Using

When using this product, do not use in or near the eyes. In case of contact, rinse eyes thoroughly with water.

Stop use and ask a doctor if irritation or rash appears and lasts.

Keep out of reach of children. If swallowed, get medical help or contact a Poison Control Center right away.

Directions

Place enough product in the palm of your hands to thoroughly cover your hands. Rub hands together briskly until product is completely absorbed and hands are dry.

Other information

Store between 15-30C (59-86F)
Avoid freezing and excessive heat above 40C (105F)

Inactive ingredients

glycerin, aloe barbadensis leaf extract, camellia sinensis (green tea) leaf extract, purified water, isopropyl alcohol, polyacrylate crosspolymer-6, rosa damascena flower water, hamamelis virginiana (witch hazel) leaf extract, citrus aurantium dulcis (orange) peel oil, filipendula ulmaria (queen of the prairie) extract, yucca schidigera root extract

Purpose

Antiseptic, Hand Sanitizer